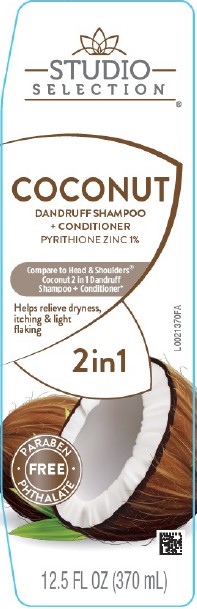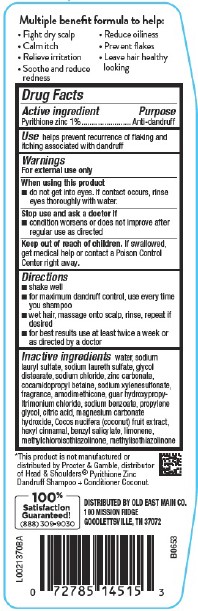 DRUG LABEL: 2 in 1 Dandruff
NDC: 55910-496 | Form: SHAMPOO
Manufacturer: Old East Main Co.
Category: otc | Type: HUMAN OTC DRUG LABEL
Date: 20260302

ACTIVE INGREDIENTS: PYRITHIONE ZINC 10 mg/1 mL
INACTIVE INGREDIENTS: WATER; SODIUM LAURYL SULFATE; SODIUM LAURETH SULFATE; GLYCOL DISTEARATE; SODIUM CHLORIDE; ZINC CARBONATE; COCAMIDOPROPYL BETAINE; SODIUM XYLENESULFONATE; AMODIMETHICONE (800 CST); GUAR HYDROXYPROPYLTRIMONIUM CHLORIDE (1.7 SUBSTITUENTS PER SACCHARIDE); SODIUM BENZOATE; PROPYLENE GLYCOL; CITRIC ACID MONOHYDRATE; MAGNESIUM CARBONATE HYDROXIDE; COCONUT; .ALPHA.-HEXYLCINNAMALDEHYDE; BENZYL SALICYLATE; LIMONENE, (+)-; METHYLCHLOROISOTHIAZOLINONE; METHYLISOTHIAZOLINONE

Studio Selection 362.000/362AA-AB
Coconut Dandruff 2 in 1 Shampoo & Conditioner

Claims

Multiple benefit formula to help:

- Fight dry scalp
- Calm itch
- Relieve irritation
- Soothe and reduce redness
- Reduce oilness
- Prevent flakes
- Leave hair healthy looking

Active Ingredient

Pyrithione zinc 1%

Purpose

Anti-dandruff

Use

helps prevent recurrence of flaking and itching associated with dandruff

Warnings

For external use only

When using this product

- do not get into eyes. If contact occurs, rinse eyes thoroughly with water.

Stop use and ask a doctor if

- condition worsens or does not improve after regular use as directed

Keep out of reach of children.

If swallowed, get medical help or contact a Poison Control Center right away.

Directions

- shake well
- for maximum dandruff control, use every time you shampoo
- wet hair, massage onto scalp, rinse, repeat if desired
- for best results use at least twice a week or as directed by a doctor

Inactive ingredients

water, sodium lauryl sulfate, sodium laureth sulfate, glycol distearate, sodium chloride, zinc carbonate, cocamidopropyl betaine, sodium xylenesulfonate, fragrance, amodimethicone, guar hydroxypropyltrimonium chloride, sodium benzoate, propylene glycol, citric acid, magnesium carbonate hydroxide, Cocos nucifera (coconut) fruit extract, hexyl cinnamal, benzyl salicylate, limonene, methylchloroisothiazolinone, methylisothiazolinone

Disclaimer

*This product is not manufactured or distributed by Procter & Gamble, distributer of Head & Shoulders® Pyrithione Zinc Dandruff Shampoo + Conditioner Coconut.

Adverse Reaction

DISTRIBUTED BY OLD EAST MAIN CO.

100 MISSION RIDGE

GOODLETTSVILLE, TN 37072

100% Satisfaction Guaranteed!

(888)309-9030

Principal Panel Display

STUDIO SELECTION®

COCONUT

DANDRUFF SHAMPOO + CONDITIONER

PYRITHIONE ZINC 1%

Compare to Head & Shoulders®Coconut 2 in 1 Dandruff + Conditioner*

Helps relieve dryness, itching & light flaking

2in1

PARABEN - PHTHALATE FREE

12.5 FL OZ (370 mL)